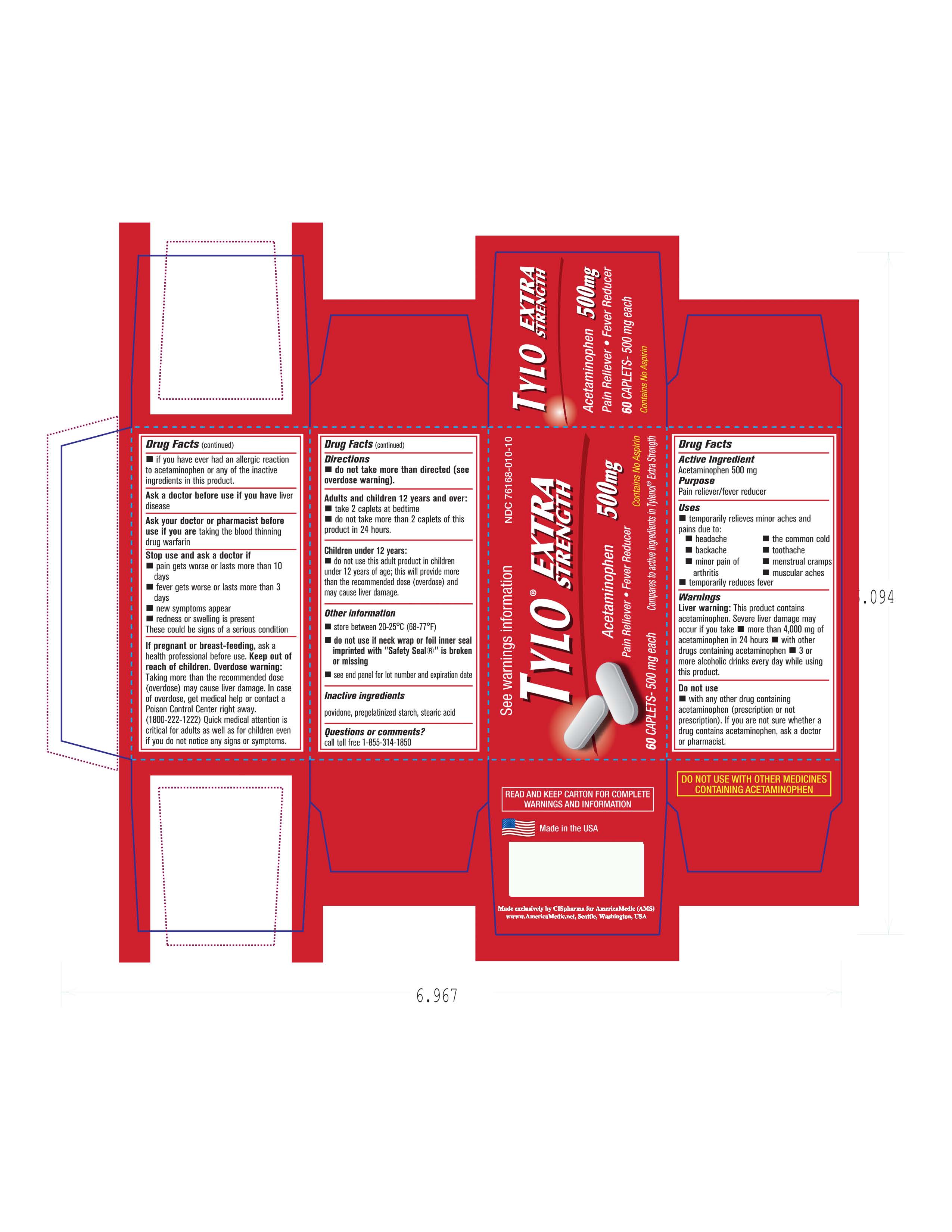 DRUG LABEL: TYLO
NDC: 49638-002 | Form: TABLET
Manufacturer: America Medic
Category: otc | Type: HUMAN OTC DRUG LABEL
Date: 20120522

ACTIVE INGREDIENTS: Acetaminophen 500 mg/1 1
INACTIVE INGREDIENTS: POVIDONE; STARCH, CORN; STEARIC ACID

DRUG FACTS

ACTIVE INGREDIENT

Acetaminophen

Keep out of reach of children. In case of overdose, get medical help right away and contact a poison control center right away.

PURPOSE

Oral Analgesic

DOSAGE AND ADMINISTRATION

Adults and children 12 years and over: Take 2 tablets at bedtime(Do not take more than 2 tablets in a 24 hour time)

INACTIVE INGREDIENT

Povidone
pregelatinized starch
stearic acid

INDICATIONS AND USAGE

Oral analgesic.

Do not use this product if you have had an allergic to Acetaminophen or any of the inactive ingredients. Ask a doctor before taking this product if you have Liver disease or are taking blood thinning medication. Do not take more than directed.If pregnant or breast feeding contact a doctor before using this product. Stop use and consult a doctor if: Pain gets worse or last more than 10 days: If fever gets worse or last more than 3 days: new symptoms appear: redness or swelling appear.

PACKAGE LABEL

image of carton